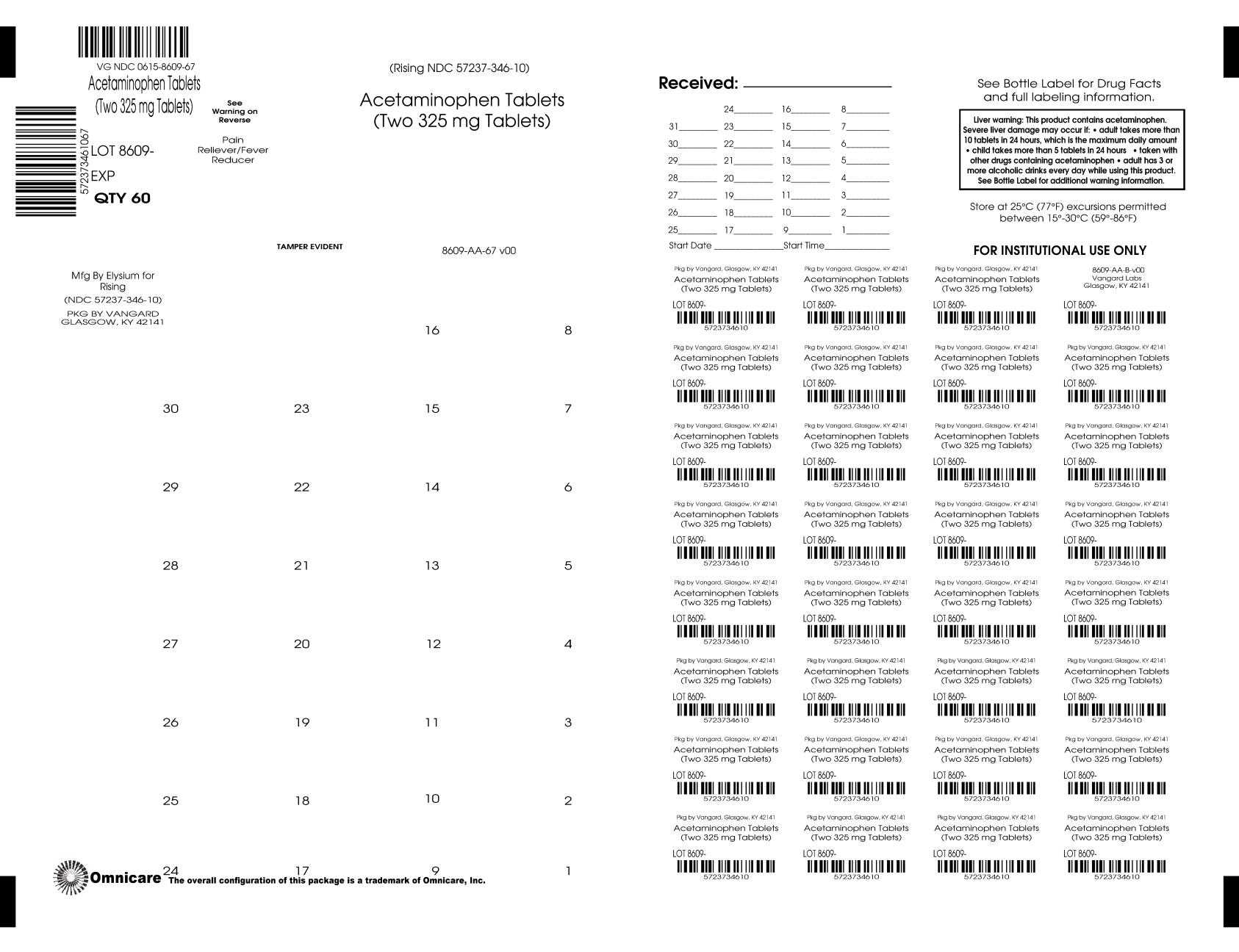 DRUG LABEL: Acetaminophen
NDC: 0615-8609 | Form: TABLET, FILM COATED
Manufacturer: NCS HealthCare of KY, LLC dba Vangard Labs
Category: otc | Type: HUMAN OTC DRUG LABEL
Date: 20260226

ACTIVE INGREDIENTS: ACETAMINOPHEN 325 mg/1 1
INACTIVE INGREDIENTS: HYPROMELLOSE, UNSPECIFIED; MAGNESIUM STEARATE; MICROCRYSTALLINE CELLULOSE; POLYETHYLENE GLYCOL, UNSPECIFIED; POVIDONE; STARCH, CORN; STEARIC ACID; TALC; TITANIUM DIOXIDE

Compare to active ingredient in Tylenol® Regular Strength†
Acetaminophen
325 mg
* Pain Reliever
* Fever Reducer
* Contains No Aspirin

DO NOT USE IF IMPRINTED SAFETY SEAL UNDER CAP IS BROKEN OR MISSING. Drug Facts

Active Ingredient (in each tablet) Purpose
Acetaminophen USP, 325 mg.................................Pain Reliever/Fever Reducer

Uses

To reduce fever and for the temporary relief of minor aches and
pains due to:

- headache
- muscular aches
- backache
- minor pain from arthritis
- the common cold
- toothache
- premenstrual and menstrual cramps
- temporarily reduces fever.

Warnings

Liver warning: This product contains acetaminophen.

Severe liver damage may occur if

- adult takes more than 10 tablets in 24 hours, which is the maximum daily amount
- child takes more than 5 tablets in 24 hours
- taken with other drugs containing acetaminophen
- adult has 3 or more alcoholic drinks every day while using this product

Do not use

- with any other drug containing acetaminophen (prescription or nonprescription). If you are not sure whether a drug contains acetaminophen, ask a doctor or pharmacist.
- if you are allergic to acetaminophen or any of the inactive ingredients in this product.

Ask a doctor before use if you have liver disease.

Ask a doctor or pharmacist before use if you are taking the blood thinning drug warfarin.
Stop use and ask a doctor if
• pain gets worse or lasts more than 10 days in adults and children.
• pain gets worse or lasts more than 5 days in children under 12 years.
• fever gets worse or lasts more than 3 days.
• new symptoms occur.
• redness or swelling is present.
These could be signs of a serious condition.

PREGNANCY OR BREAST FEEDING

If pregnant or breast-feeding, ask a health professional before use.

Keep out of reach of children.
Overdose warning:
Taking more than the recommended dose (overdose) may cause liver damage. In case of overdose, get medical help or contact a Poison Control Center right away (1-800-222-1222). Prompt medical attention is critical for adults as well as for children even if you do not notice any signs or symptoms.

Directions

Do not take more than directed
Adults and Children 12 years and over:

- take 2 tablets every 4 to 6 hours while symptoms last.
- do not take more than 10 tablets in 24 hours.
- do not take for more than 10 days unless directed by a doctor

Children 6 years to under 12 years:

- take 1 tablet every 4 to 6 hours while symptoms last.
- do not take more than 5 tablets in 24 hours.
- do not use for more than 5 days unless directed by a doctor

Children under 6 years:
ask a doctor

Other Information

- SODIUM FREE
- store at 25°C (77°F) excursions permitted between 15°-30°C (59°-86°F)
- see end panel for lot number and expiration date.

Inactive Ingredients

Hypromellose, magnesium stearate, microcrystalline cellulose, polyethylene glycol, povidone, pregelatinized starch, stearic acid, talc, titanium dioxide.

Questions and Comments? Call 1-844-474-7464

Distributed by:

Rising Pharma Holdings, Inc.

East Brunswick, NJ 08816

Made in India

Mfg. Lic. No.: G/25/2258

Issued: 07/2025 (S-069-00)

†This product is not manufactured or distributed by Johnson & Johnson Consumer Inc., McNeil Consumer Healthcare Division, owner of the registered trademark Tylenol® Regular strength.